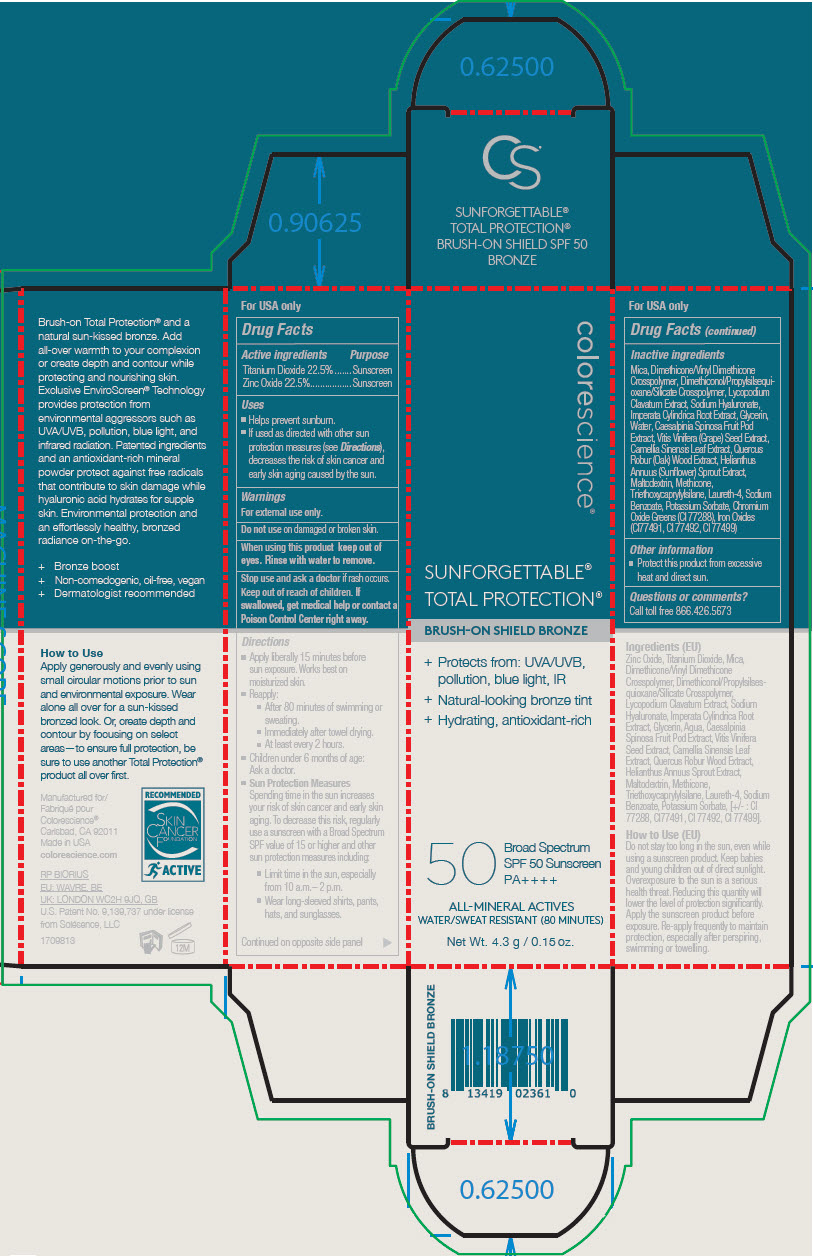 DRUG LABEL: Sunforgettable Total Protection Brush-On Shield SPF 50
NDC: 68078-027 | Form: POWDER
Manufacturer: Colorescience
Category: otc | Type: HUMAN OTC DRUG LABEL
Date: 20241216

ACTIVE INGREDIENTS: Titanium Dioxide 225 mg/1 g; Zinc Oxide 225 mg/1 g
INACTIVE INGREDIENTS: Mica; Dimethicone/Vinyl Dimethicone Crosspolymer (Hard Particle); Dimethiconol/Propylsilsesquioxane/Silicate Crosspolymer (450000000 MW); Maltodextrin; Methicone (20 CST); Glycerin; Laureth-4; Hyaluronate Sodium; Imperata Cylindrica Root; Water; Triethoxycaprylylsilane; Vitis Vinifera Seed; Green Tea Leaf; Quercus Robur Twig Bark; TARA SPINOSA RESIN; Sunflower Oil; Potassium Sorbate; Sodium Benzoate; Ferric Oxide Yellow; Ferrosoferric Oxide; Ferric Oxide Red; Chromic Oxide

Sunforgettable® Total Protection™ Brush-On Shield SPF 50

Drug Facts

ACTIVE INGREDIENT

Active ingredients | Purpose
Titanium Dioxide 22.5% | Sunscreen
Zinc Oxide 22.5% | Sunscreen

Uses

- Helps prevent sunburn.
- If used as directed with other sun protection measures (see Directions), decreases the risk of skin cancer and early skin aging caused by the sun.

Warnings

For external use only.

Do not use on damaged or broken skin.

When using this product keep out of eyes. Rinse with water to remove.

Stop use and ask a doctor if rash occurs.

Keep out of reach of children.

If swallowed, get medical help or contact a Poison Control Center right away.

Directions

- Apply liberally 15 minutes before sun exposure. Works best on moisturized skin.
- Reapply:
  - After 80 minutes of swimming or sweating.
  - Immediately after towel drying.
  - At least every 2 hours.
- Children under 6 months of age:
  Ask a doctor.
- Sun Protection Measures
  Spending time in the sun increases your risk of skin cancer and early skin aging. To decrease this risk, regularly use a sunscreen with a Broad Spectrum SPF value of 15 or higher and other sun protection measures including:
  - Limit time in the sun, especially from 10 a.m.– 2 p.m.
  - Wear long-sleeved shirts, pants, hats, and sunglasses.

Inactive ingredients

Mica, Dimethicone/Vinyl Dimethicone Crosspolymer, Dimethiconol/Propylsilsequioxane/Silicate Crosspolymer, Lycopodium Clavatum Extract, Sodium Hyaluronate, Imperata Cyclindrica Root Extract, Glycerin, Water, Caesalpinia Spinosa Fruit Pod Extract, Vitis Vinifera (Grape) Seed Extract, Camellia Sinensis Leaf Extract, Quercus Robur (Oak) Wood Extract, Helianthus Annuus (Sunflower) Sprout Extract, Maltodextrin, Methicone, Triethoxycaprylylsilane, Laureth-4, Sodium Benzoate, Potassium Sorbate, Chromium Oxide Greens (CI 77288), Iron Oxides (CI77491, CI 77492, CI 77499)

Other information

- Protect this product from excessive heat and direct sun.

Questions or comments?

Call toll free 866.426.5673

Distributed in USA by
colorescience®
Carlsbad, CA 92011

PRINCIPAL DISPLAY PANEL - 4.3 g Tube Carton

colorescience®

SUNFORGETTABLE®
TOTAL PROTECTION®

BRUSH-ON SHIELD BRONZE

+ Protects from: UVA/UVB,
  pollution, blue light, IR
+ Natural-looking bronze tint
+ Hydrating, antioxidant-rich

50
Broad Spectrum
SPF 50 Sunscreen
PA++++

ALL-MINERAL ACTIVES
WATER/SWEAT RESISTANT (80 MINUTES)

Net Wt. 4.3 g / 0.15 oz.